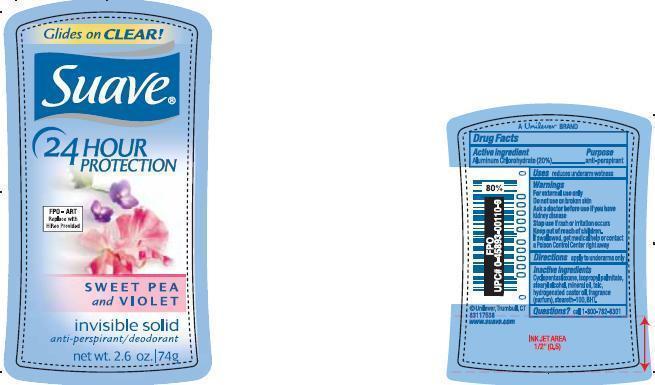 DRUG LABEL: Suave Sweet Pea and Violet
NDC: 64942-0893 | Form: STICK
Manufacturer: Conopco Inc. d/b/a Unilever
Category: otc | Type: HUMAN OTC DRUG LABEL
Date: 20131025

ACTIVE INGREDIENTS: Aluminum Chlorohydrate 20 g/100 g
INACTIVE INGREDIENTS: CYCLOMETHICONE 5; ISOPROPYL PALMITATE; STEARYL ALCOHOL; MINERAL OIL; TALC; HYDROGENATED CASTOR OIL; STEARETH-100; BUTYLATED HYDROXYTOLUENE

PDP and Drug facts box text for Suave Sweet Pea and Violet Antiperspirant and Deodorant

Active ingredient

Aluminum Chlorohydrate (20%)

Purpose

antiperspirant

Uses

reduces underarm wetness

Warnings

For external use only

Do not use on broken skin

Ask a doctor before use if you have kidney disease

Stop use if rash or irritation occurs

Keep out of reach of children. If swallowed, get medical help or contact a Poison Control Center right away.

Directions

apply to underarms only

Inactive Ingredients
Cyclopentasiloxane, Isopropyl Palmitate, Stearyl Alcohol, Mineral Oil, Talc, Hydrogenated Castor Oil, Fragrance (Parfum), Steareth-100, BHT.

Questions?
Call 1-800-782-8301